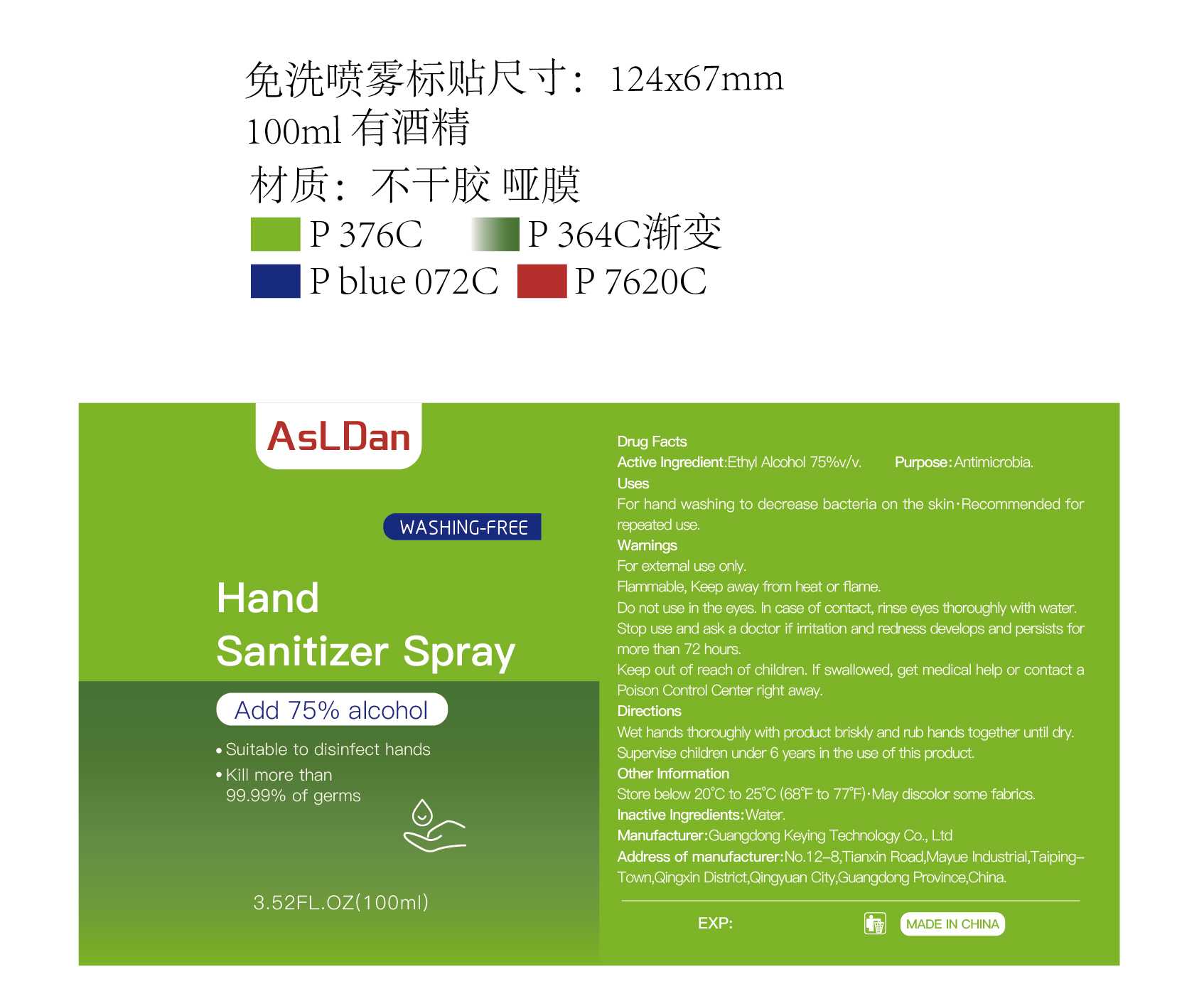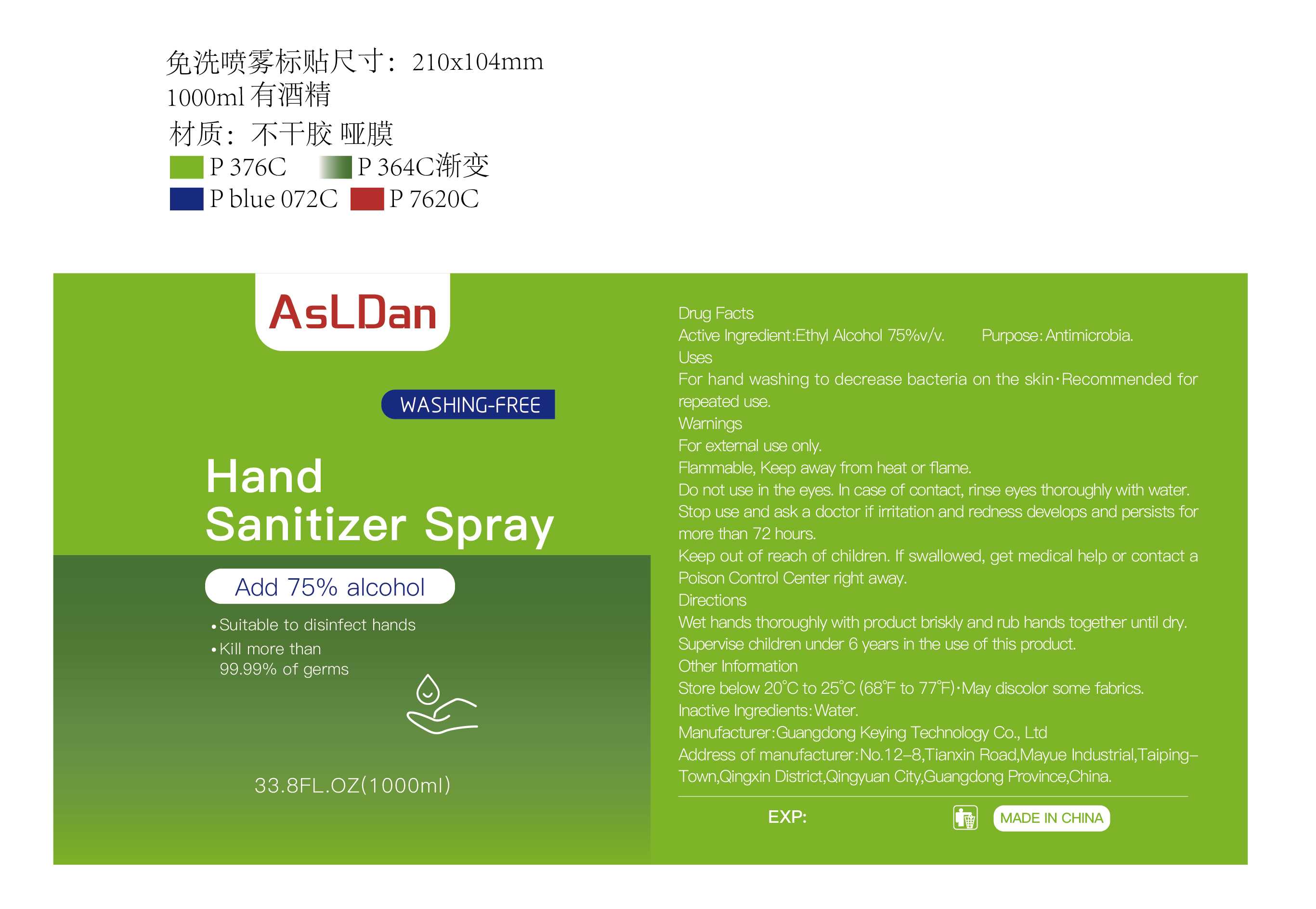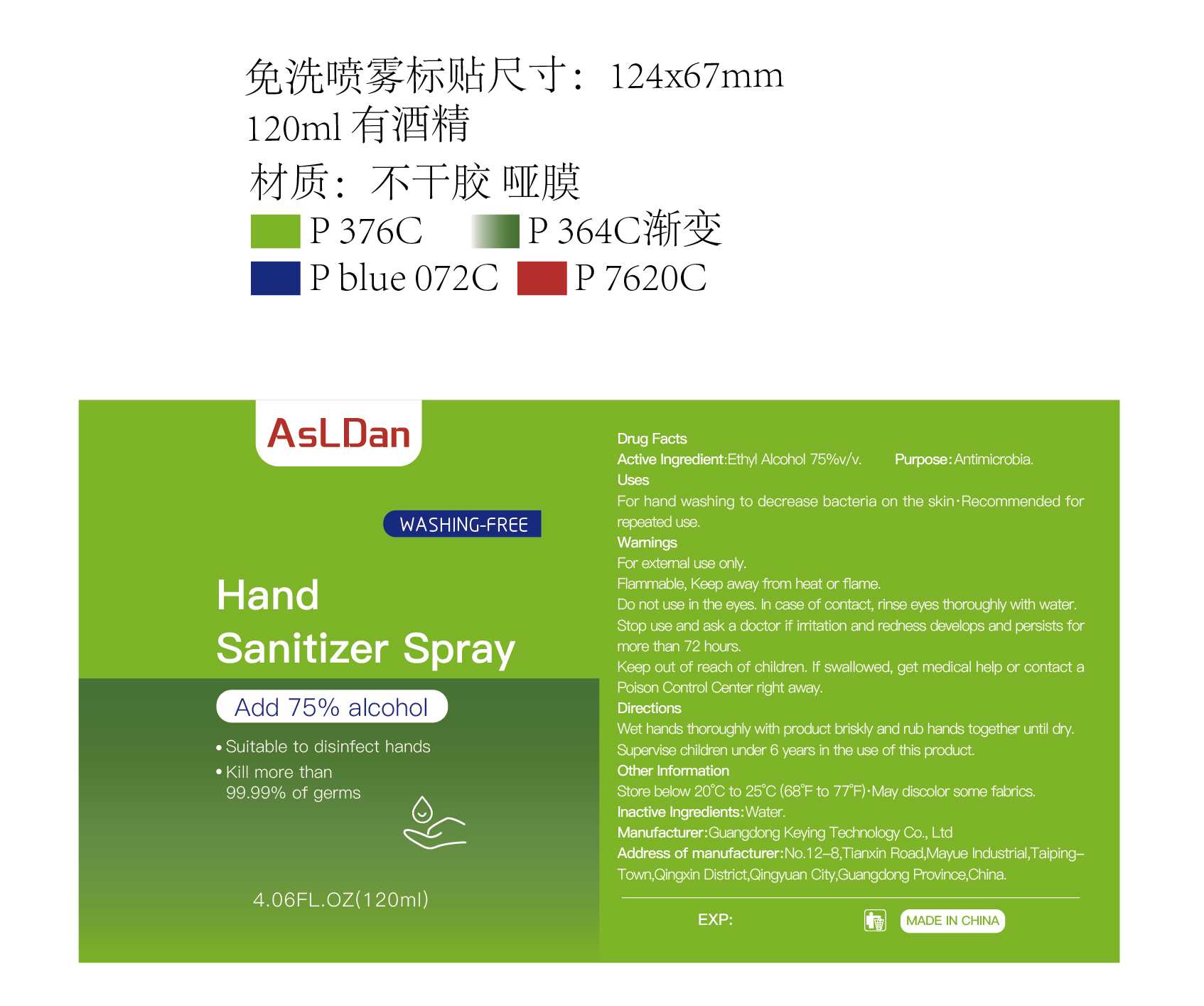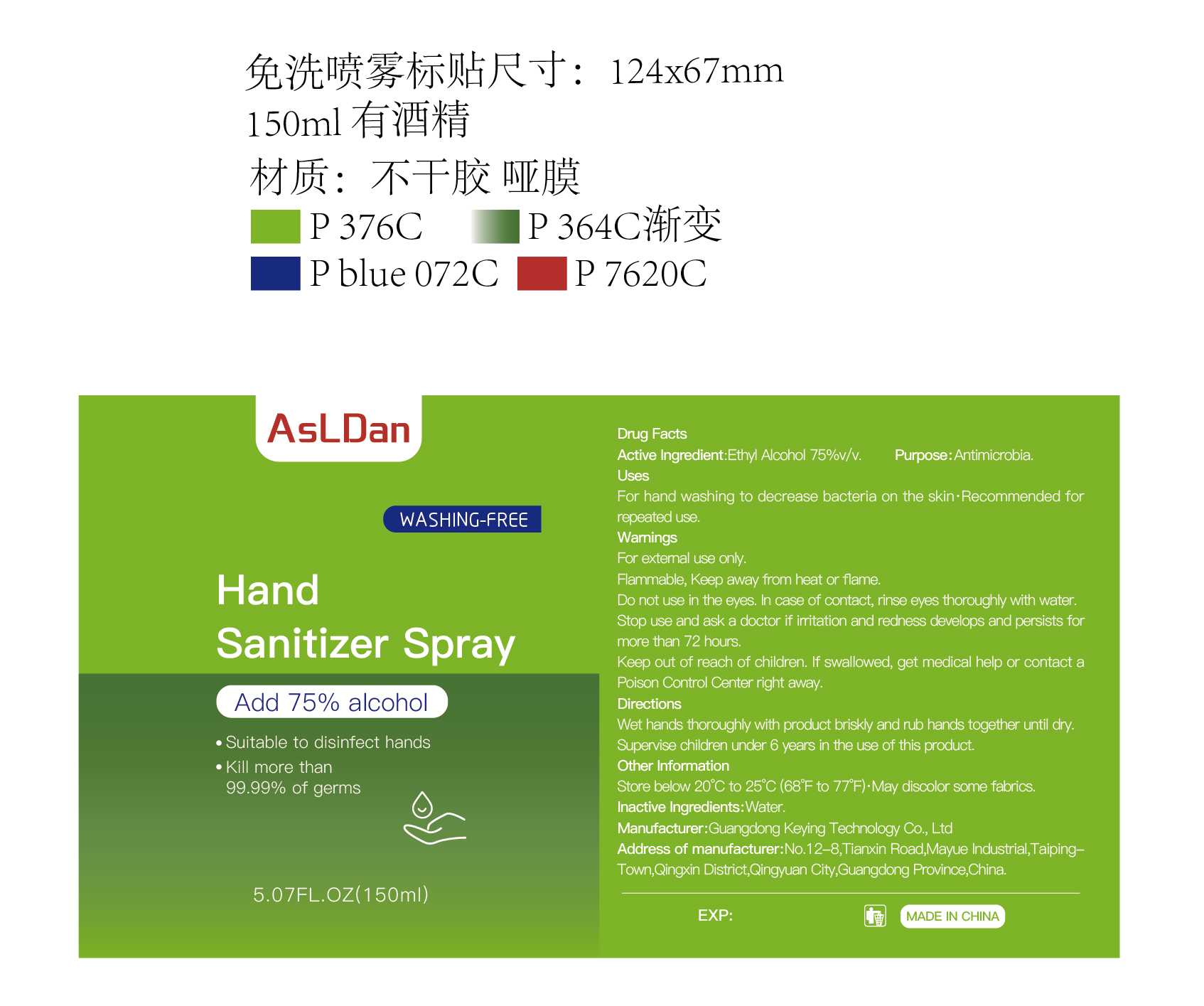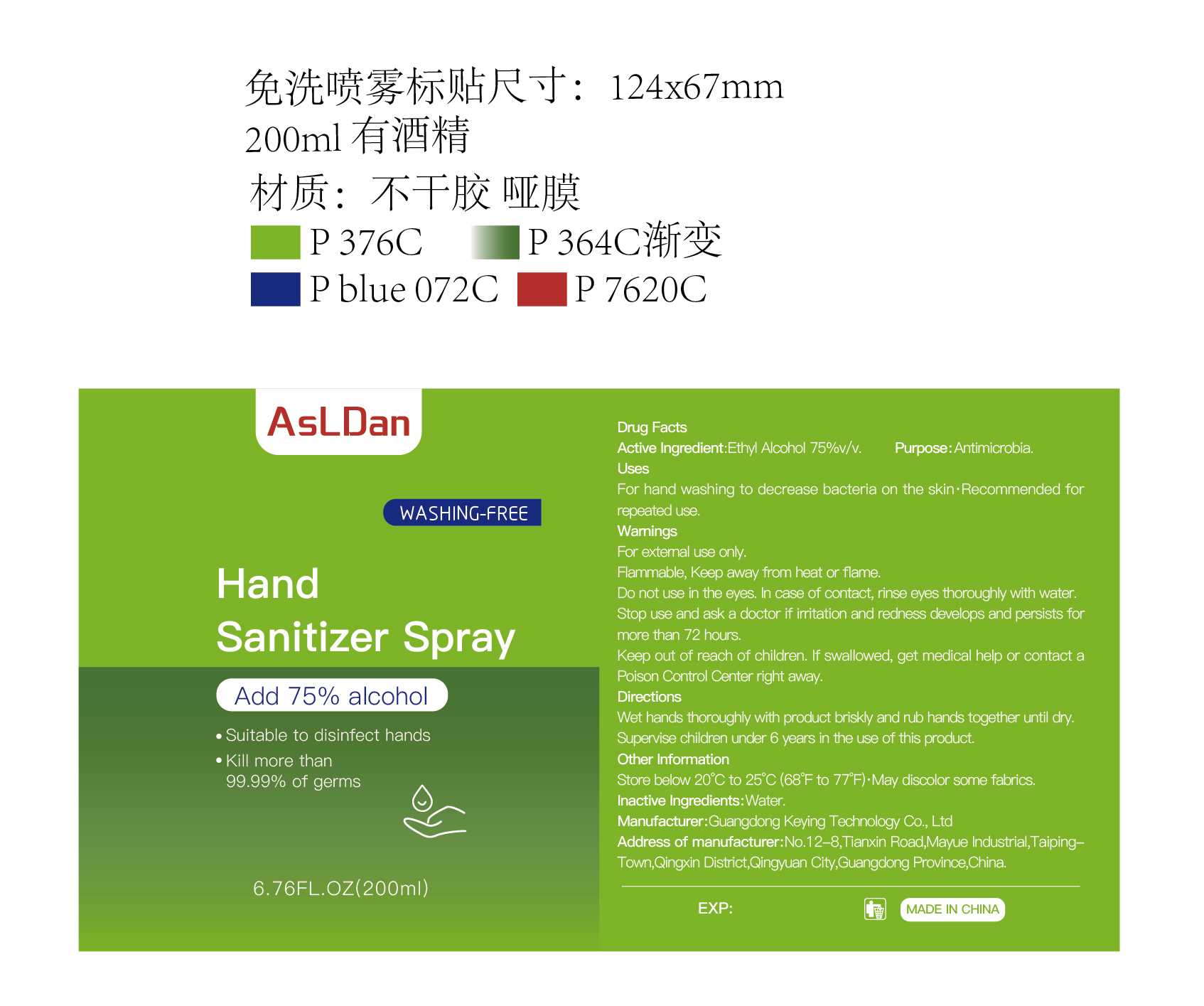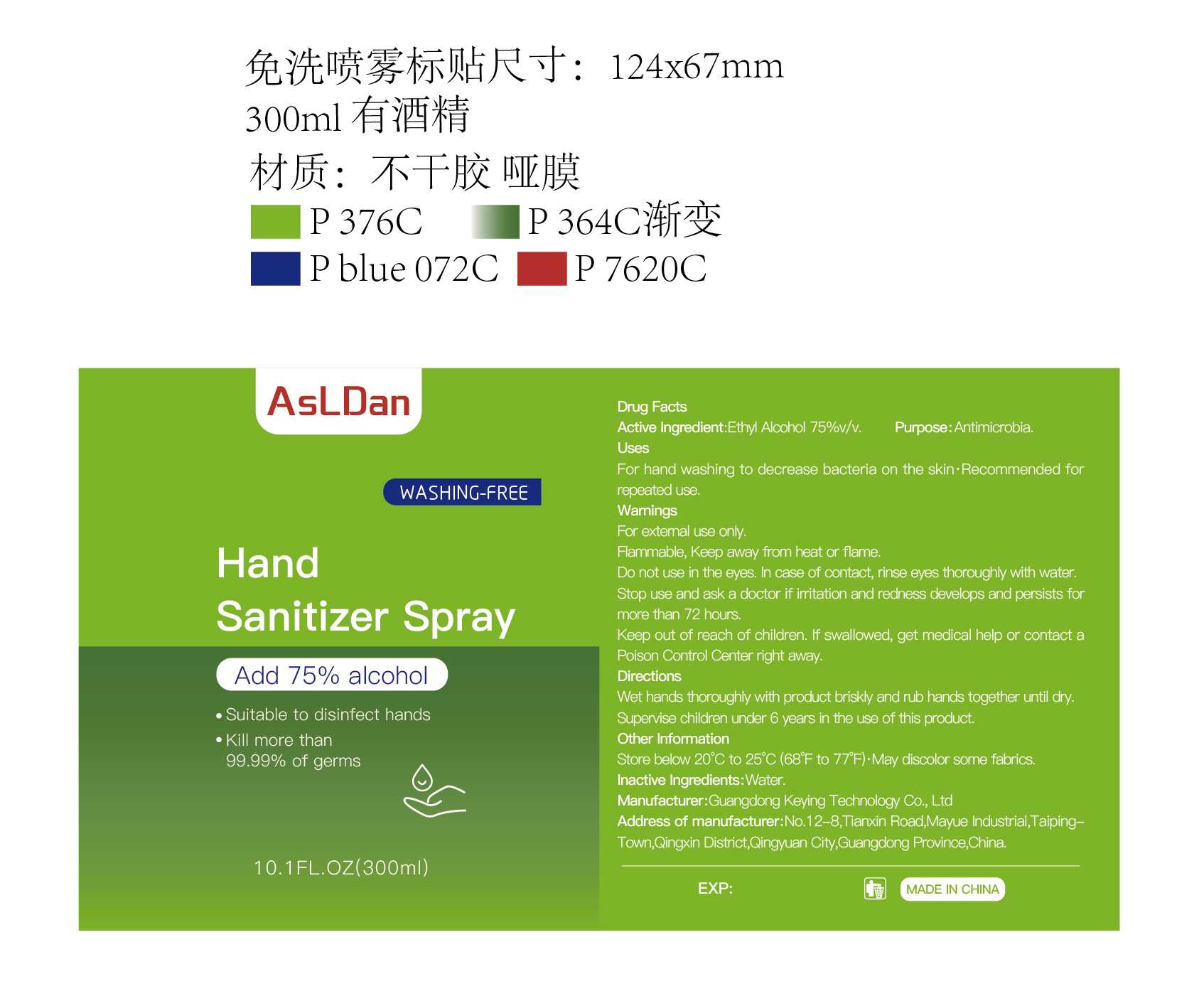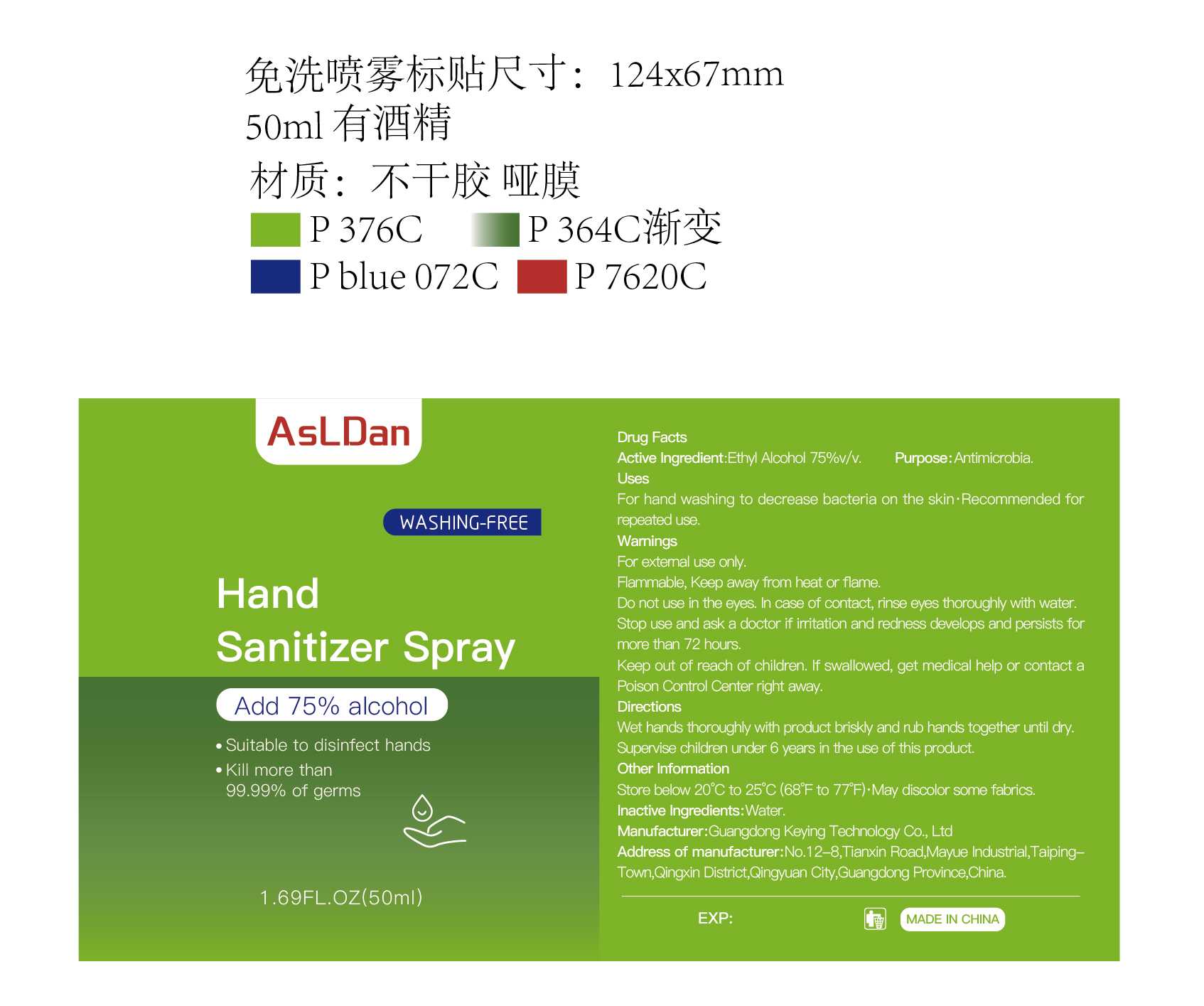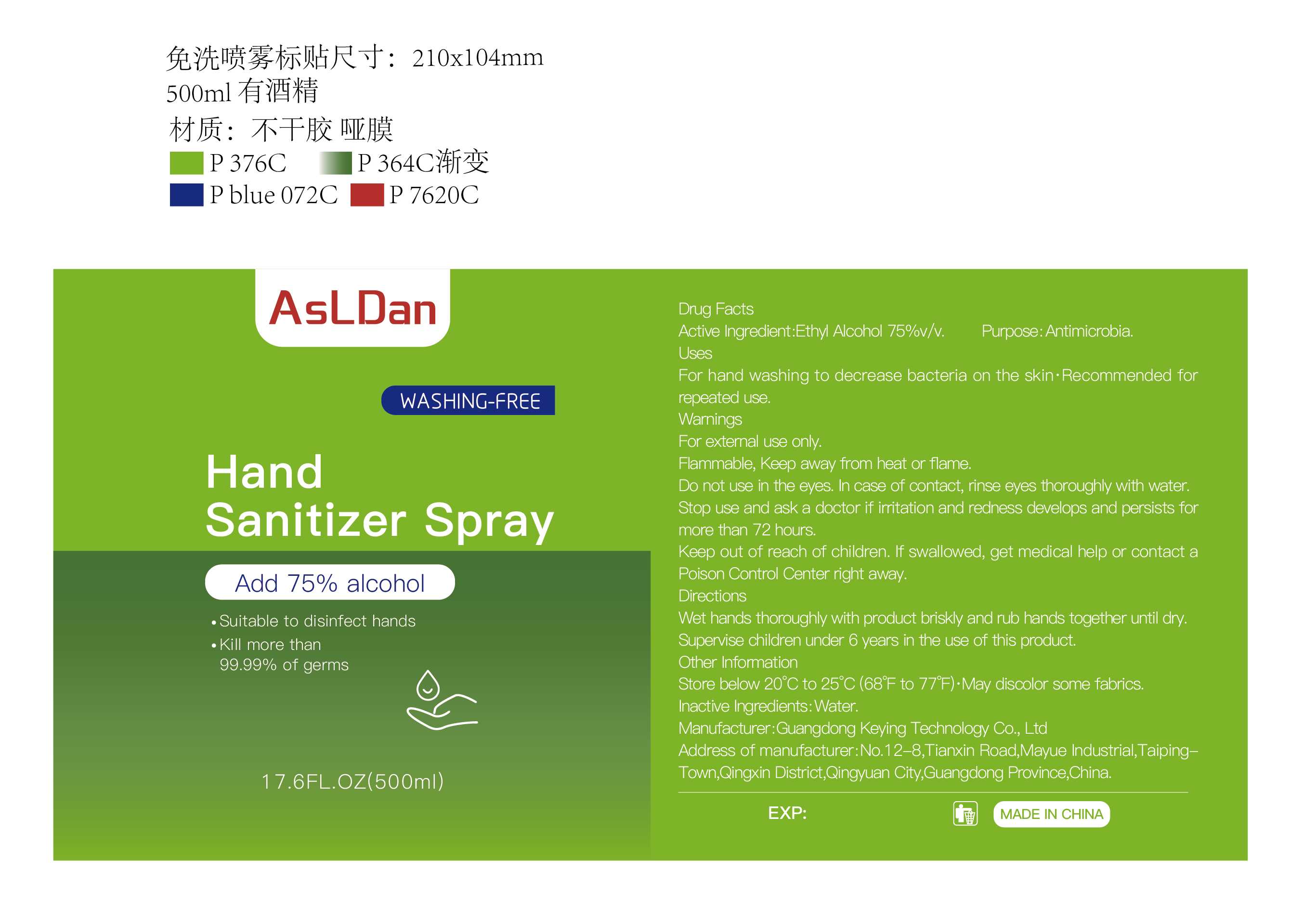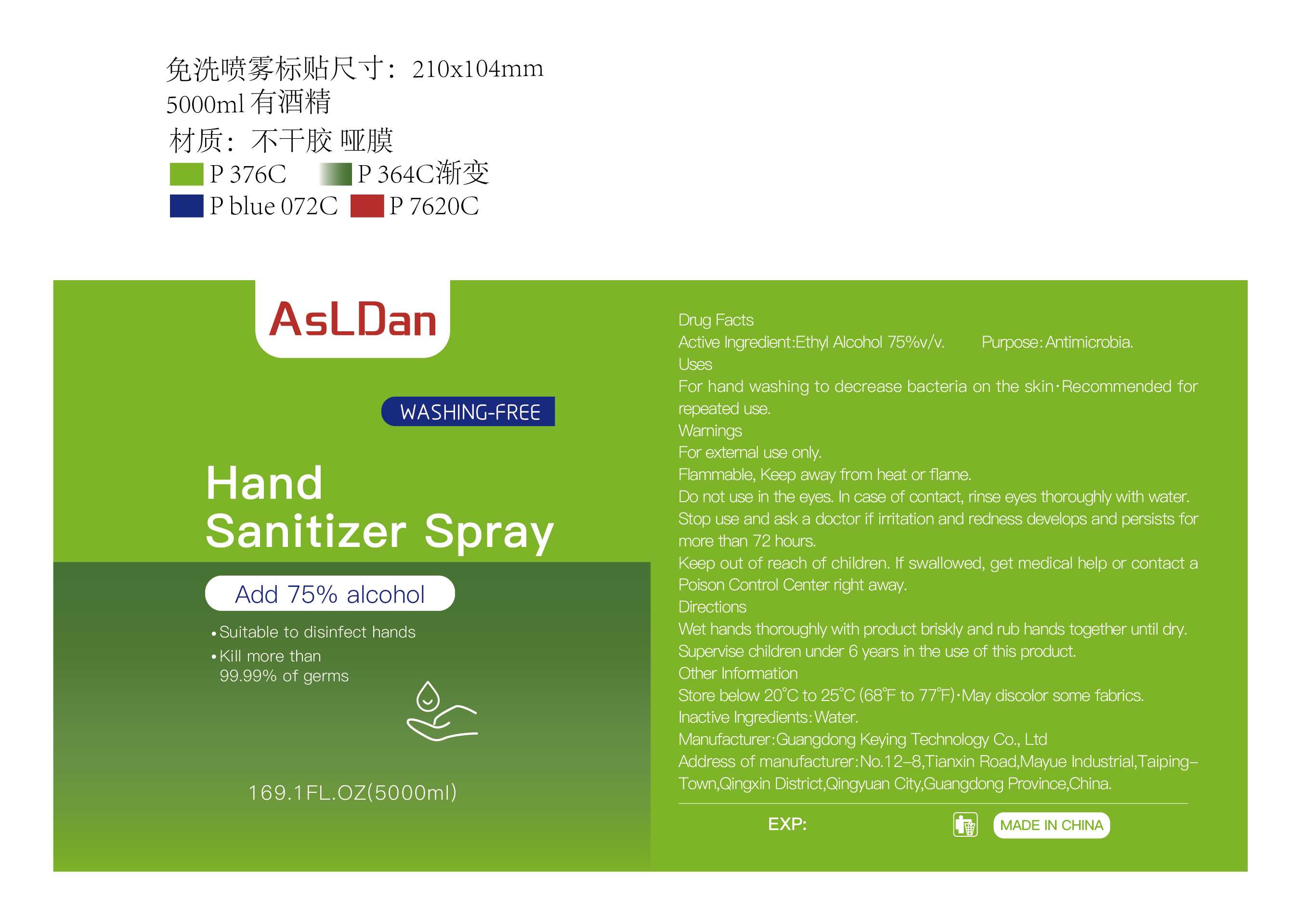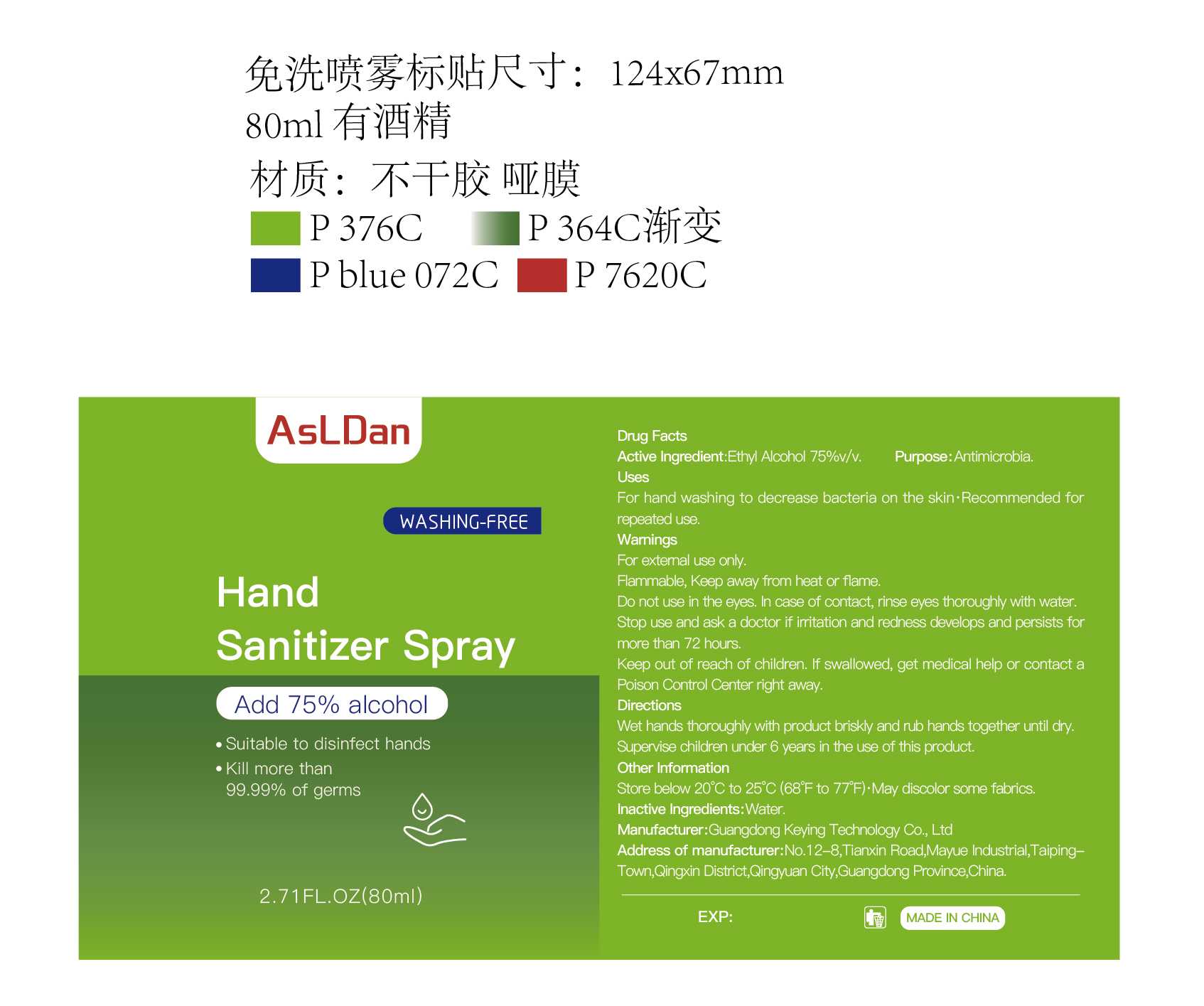 DRUG LABEL: ASLDAN Hand disinfection
NDC: 79865-002 | Form: SPRAY
Manufacturer: Guangdong Keying Technology Co., Ltd
Category: otc | Type: HUMAN OTC DRUG LABEL
Date: 20200727

ACTIVE INGREDIENTS: ALCOHOL 75 mL/100 mL
INACTIVE INGREDIENTS: WATER

ASLDAN Hand disinfection spray

Active Ingredient(s)

Ethyl Alcohol 75% v/v

Purpose

Antimicrobia

Use

For hand washing to decrease bacteria on the skin· Recommended for repeated use.

Warnings

For external use only.
Flammable, Keep away from heat or flame.

Do not use in the eyes. In case of contact，rinse eyes thoroughly with water.

WHEN USING

/

Stop use and ask a doctor if irritation and redness develops and persists for more than 72 hours.

Keep out of reach of children. If swallowed, get medical help or contact a Poison Control Center right away.

Directions

Wet hands thoroughly with product briskly and rub hands together until dry
Supervise children under 6 years in the use of this product

Inactive ingredients

Water